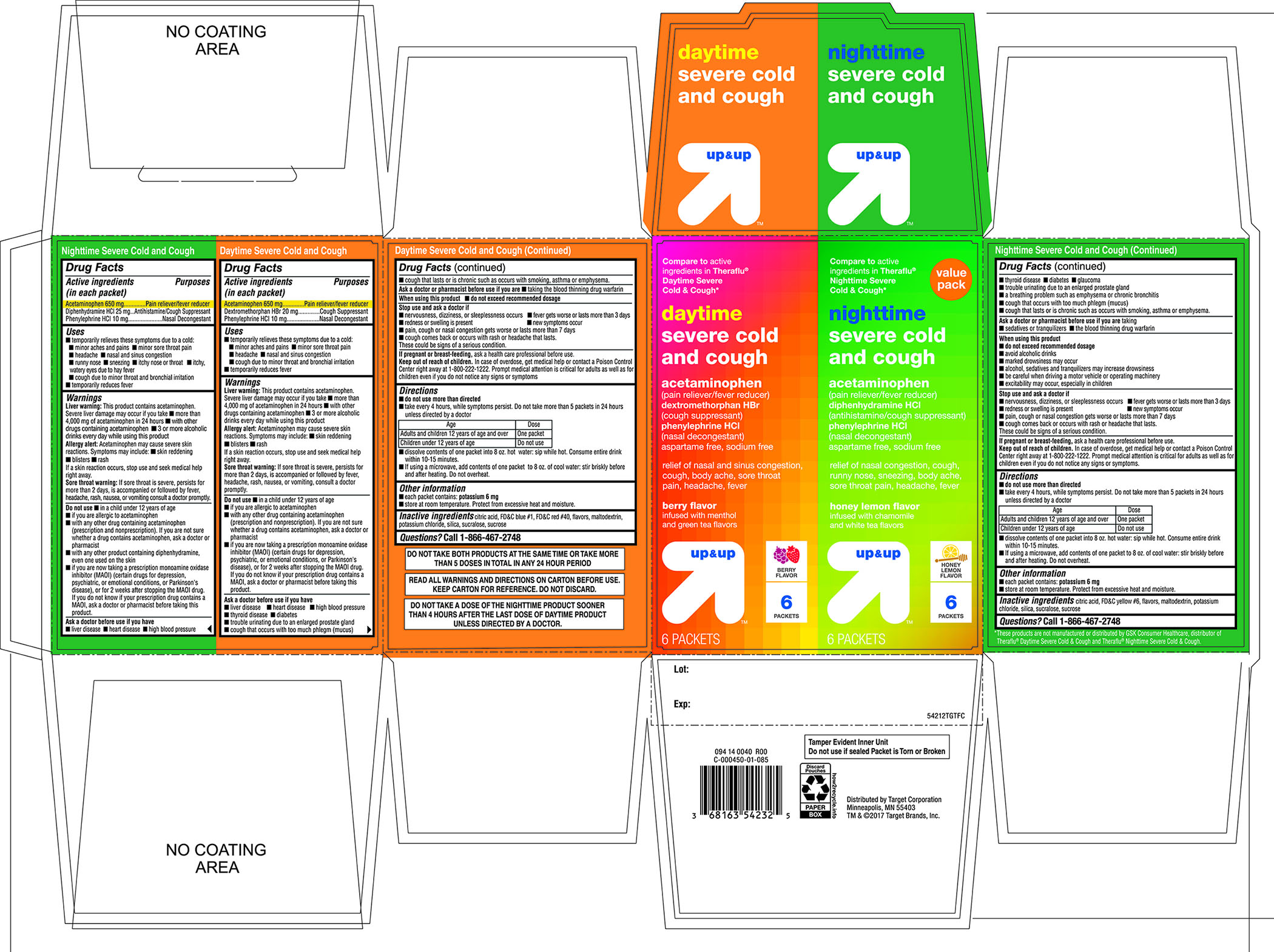 DRUG LABEL: daytime severe cold and cough and nighttime severe cold and cough
NDC: 11673-542 | Form: KIT | Route: ORAL
Manufacturer: Target Corporation
Category: otc | Type: HUMAN OTC DRUG LABEL
Date: 20180118

ACTIVE INGREDIENTS: ACETAMINOPHEN 650 mg/1 1; DEXTROMETHORPHAN HYDROBROMIDE 20 mg/1 1; PHENYLEPHRINE HYDROCHLORIDE 10 mg/1 1; ACETAMINOPHEN 650 mg/1 1; DIPHENHYDRAMINE HYDROCHLORIDE 25 mg/1 1; PHENYLEPHRINE HYDROCHLORIDE 10 mg/1 1
INACTIVE INGREDIENTS: FD&C BLUE NO. 1; ANHYDROUS CITRIC ACID; MALTODEXTRIN; POTASSIUM CHLORIDE; FD&C RED NO. 40; SILICON DIOXIDE; SUCRALOSE; SUCROSE; ANHYDROUS CITRIC ACID; MALTODEXTRIN; POTASSIUM CHLORIDE; SILICON DIOXIDE; SUCRALOSE; SUCROSE; FD&C YELLOW NO. 6

daytime severe cold and cough & nighttime severe cold and cough value pack

Active ingredients (in each packet) – Daytime Severe Cold and Cough

Acetaminophen 650 mg

Dextromethorphan HBr 20 mg

Phenylephrine HCl 10 mg

Active ingredients (in each packet) - Nighttime Severe Cold and Cough

Acetaminophen 650 mg

Diphenhydramine HCl 25 mg

Phenylephrine HCl 10 mg

Purposes - Daytime Severe Cold and Cough

Pain reliever/fever reducer

Cough Suppressant

Nasal Decongestant

Purpose - Nighttime Severe Cold and Cough

Pain reliever/fever reducer

Antihistamine/cough Suppressant

Nasal Decongestant

Uses - Daytime Severe Cold and Cough

- temporarily relieves these symptoms due to a cold:
- minor aches and pains
- minor sore throat pain
- headache
- nasal and sinus congestion
- cough due to minor throat and bronchial irritation
- temporarily reduces fever

Uses - Nighttime Severe Cold and Cough

- temporarily relieves these symptoms due to a cold:
- minor aches and pains
- minor sore throat pain
- headache
- nasal and sinus congestion
- runny nose
- sneezing
- itchy nose or throat
- itchy, watery eyes due to hay fever
- cough due to minor throat and bronchial irritation
- temporarily reduces fever

Warnings – Daytime Severe Cold and Cough and Nighttime Severe Cold and Cough

Liver warning: This product contains acetaminophen. Severe liver damage may occur if you take

- more than 4,000 mg of acetaminophen in 24 hours
- with other drugs containing acetaminophen
- 3 or more alcoholic drinks every day while using this product
  Allergy alert: Acetaminophen may cause severe skin reactions. Symptoms may include:
  ●Skin reddening● blisters● rash
  Is a skin reaction occurs, stop use and seek medical help right away.

Sore throat warning: If sore throat is severe, persists for more than 2 days, is accompanied or followed by fever, headache, rash, nausea, or vomiting, consult a doctor promptly.

Do not use - Daytime Severe Cold and Cough

- in a child under 12 years of age
- if you are allergic to acetaminophen
- with any other drug containing acetaminophen (prescription or nonprescription). If you are not sure whether a drug contains acetaminophen, ask a doctor or a pharmacist.
- if you are now taking a prescription monoamine oxidase inhibitor (MAOI) (certain drugs for depression, psychiatric, or emotional conditions, or Parkinson's disease), or for 2 weeks after stopping the MAOI drug. If you do not know if your prescription drug contains an MAOI, ask a doctor or pharmacist before taking this product.

Do not use - Nighttime Severe Cold and Cough

- in a child under 12 years of age
- if you are allergic to acetaminophen
- with any other drug containing acetaminophen (prescription or nonprescription). If you are not sure whether a drug contains acetaminophen, ask a doctor or a pharmacist.
- with any other product containing diphenhydramine, even one used on skin
- if you are now taking a prescription monoamine oxidase inhibitor (MAOI) (certain drugs for depression, psychiatric, or emotional conditions, or Parkinson’s disease), or for 2 weeks after stopping the MAOI drug. If you do not know if your prescription drug contains a MAOI, ask a doctor or pharmacist before taking this product.

Ask a doctor before use if you have - Daytime Severe Cold and Cough

- liver disease
- heart disease
- high blood pressure
- thyroid disease
- diabetes
- trouble urinating due to an enlarged prostate gland
- cough that occurs with too much phlegm (mucus)
- cough that lasts or is chronic such as occurs with smoking, asthma, or emphysema

Ask a doctor before use if you have - Nighttime Severe Cold and Cough

- liver disease
- heart disease
- high blood pressure
- thyroid disease
- diabetes
- glaucoma
- trouble urinating due to an enlarged prostate gland
- a breathing problem such as emphysema or chronic bronchitis
- cough that occurs with too much phlegm (mucus)
- cough that lasts or is chronic such as occurs with smoking, asthma, or emphysema

Ask a doctor or pharmacist before use if you are - Daytime Severe Cold and Cough

taking the blood thinning drug warfarin

Ask a doctor or pharmacist before use if you are - Nighttime Severe Cold and Cough

- taking sedatives or tranquilizers
- taking the blood thinning drug warfarin

When using this product - Daytime Severe Cold and Cough

do not exceed recommended dosage

When using this product - Nighttime Severe Cold and Cough

- do not exceed recommended dosage
- avoid alcoholic drinks
- marked drowsiness may occur
- alcohol, sedatives, and tranquilizers may increase drowsiness
- be careful when driving a motor vehicle or operating machinery
- excitability may occur, especially in children

Stop use and ask a doctor if – Daytime Severe Cold and Cough /Nighttime Severe Cold and Cough

- nervousness, dizziness, or sleeplessness occurs
- fever gets worse or lasts more than 3 days
- redness or swelling is present
- new symptoms occur
- pain, cough or nasal congestion gets worse or lasts more than 7 days
- cough comes back or occurs with rash or headache that lasts. These could be signs of a serious condition.

If pregnant or breast-feeding,

ask a health professional before use.

Keep out of reach of children.

In case of overdose, get medical help or contact a Poison Control Center right away (1-800-222-1222). Prompt medical attention is critical for adults as well as for children even if you do not notice any signs or symptoms.

Directions – Daytime Severe Cold and Cough

- do not use more than directed
- take every 4 hours, while symptoms persist, Do not take more than 5 packets in 24 hours unless directed by a doctor

Age | Dose
Adults and children 12 years of age and over | One packet
Children under 12 years of age | Do not use

- dissolve contents of one packet into 8 oz. hot water: sip while hot. Consume entire drink within 10-15 minutes.
- if using a microwave, add contents of one packet to 8 oz. of cool water: stir briskly before and after heating. Do not overheat

Directions Nighttime Severe Cold and Cough

- do not use more than directed
- take every 4 hours, while symptoms persist, Do not take more than 5 packets in 24 hours unless directed by a doctor.

Age | Dose
Adults and children 12 years of age and over | One packet
Children under 12 years of age | Do not use

- dissolve contents of one packet into 8 oz. hot water: sip while hot. Consume entire drink within 10-15 minutes.
- if using a microwave, add contents of one packet to 8 oz. of cool water: stir briskly before and after heating. Do not overheat

Other information - Daytime Severe Cold and Cough

- each packet contains: potassium 6 mg
- store at room temperature. Protect from excessive heat and moisture

Other information - Nighttime Severe Cold and Cough

- each packet contains: potassium 6 mg
- store at room temperature. Protect from excessive heat and moisture

Inactive ingredients - Daytime Severe Cold and Cough

citric acid ,FD&C blue#1, FD&C red 40#, flavors, maltodextrin, potassium chloride, silica, sucralose, sucrose

Inactive ingredients - Nighttime Severe Cold and Cough

citric acid, FD & C yellow #6, flavors, maltodextrin, potassium chloride, silica ,sucralose, sucrose,

Questions or comments?

1-866-467-2748

Package/Label Principal Display Panel

Compare to active ingredients in Theraflu® Daytime Severe Cold and Cough and Nighttime Severe Cold & Cough*

Value pack

daytime severe cold and cough

acetaminophen(pain reliever/ fever reducer)

dextromethorphan HBr (cough suppressant)

phenylephrine HCl (nasal decongestant)

aspartame free, sodium free

relief of nasal and sinus congestion,, cough ,body ache, sore throat pain, headache ,fever

berry flavor

infused with menthol and green tea flavors

6 PACKETS

nighttime severe cold and cough

acetaminophen –(pain reliever/ fever reducer)

diphenhydramine HCl – (antihistamine/ cough suppressant)

phenylephrine HCl – (nasal decongestant)

aspartame free, sodium free

relief of nasal congestion,, cough ,runny nose, sneezing, body ache, sore throat pain, headache ,fever

honey lemon flavor infused with chamomile & white tea flavors

6 PACKETS

READ ALL WARNINGS AND DIRECTIONS ON CARTON BEFORE USE .KEEP CARTON FOR REFERENCE, DO NOT DISCARD.

DO NOT TAKE BOTH PRODUCTS AT THE SAME TIME OR TAKE MORE THAN 5 DOSES IN TOTAL IN ANY 24 –HOUR PERIOD.

DO NOT TAKE A DOSE OF THE NIGHTTIME PRODUCT SOONER THAN 4 HOURS AFTER THE LAST DOSE OF DAYTIME PRODUCT UNLESS DIRECTED BY DOCTOR.

*These Products are not manufactured or distributed by GSK Consumer Healthcare, distributor of Theraflu Daytime Severe Cold & Cough and Theraflu Nighttime severe Cold & Cough

Distributed by: Target Corporation.

Minneapolis, MN 55403

TM &©2017 Target Brands, Inc.

Tamper Evident Inner Unit

Do not use if sealed packet is Torn or Broken